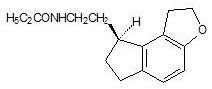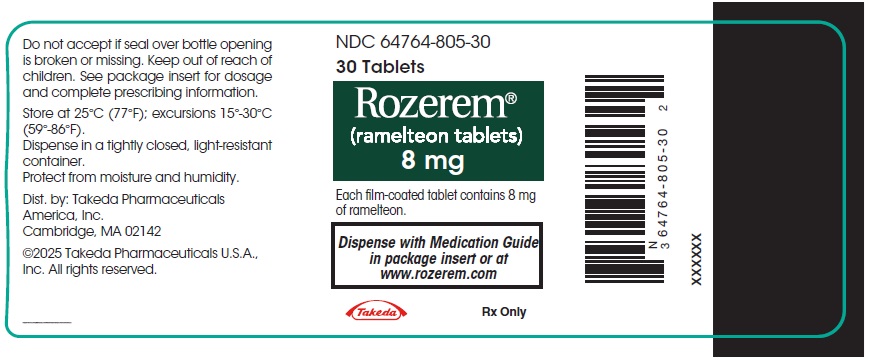 DRUG LABEL: Rozerem
NDC: 64764-805 | Form: TABLET, FILM COATED
Manufacturer: Takeda Pharmaceuticals America, Inc.
Category: prescription | Type: HUMAN PRESCRIPTION DRUG LABEL
Date: 20250715

ACTIVE INGREDIENTS: ramelteon 8 mg/1 1

HIGHLIGHTS OF PRESCRIBING INFORMATION

These highlights do not include all the information needed to use ROZEREM® safely and effectively. See full prescribing information for ROZEREM.
ROZEREM (ramelteon) tablets, for oral use
Initial U.S. Approval: 2005

1 INDICATIONS AND USAGE

ROZEREM is indicated for the treatment of insomnia characterized by difficulty with sleep onset. (1)

2 DOSAGE AND ADMINISTRATION

- Adult dose: 8 mg taken within 30 minutes of going to bed. (2.1)
- Should not be taken with or immediately after a high-fat meal. (2.1)
- Total daily dose should not exceed 8 mg. (2.1)

3 DOSAGE FORMS AND STRENGTHS

8 mg tablets. (3)

4 CONTRAINDICATIONS

- History of angioedema while taking ROZEREM. (4)
- Fluvoxamine (strong CYP1A2 inhibitor): Increases AUC for ramelteon and should not be used in combination. (7.1)

5 WARNINGS AND PRECAUTIONS

- Severe anaphylactic/anaphylactoid reactions: Angioedema and anaphylaxis have been reported. Do not rechallenge if such reactions occur. (5.1)
- Need to evaluate for comorbid diagnoses: Reevaluate if insomnia persists after 7 to 10 days of treatment. (5.2)
- Abnormal thinking, behavioral changes, complex behaviors: May include "sleep-driving" and hallucinations. Immediately evaluate any new onset behavioral changes. (5.3)
- Depression: Worsening of depression or suicidal thinking may occur. (5.3)
- CNS effects: Potential impairment of activities requiring complete mental alertness such as operating machinery or driving a motor vehicle, after ingesting the drug. (5.4)
- Reproductive effects: Include decreased testosterone and increased prolactin levels. Effect on reproductive axis in developing humans is unknown. (5.5)
- Patients with severe sleep apnea: ROZEREM is not recommended for use in this population. (5.6)

6 ADVERSE REACTIONS

Most common adverse reactions (≥3% and more common than with placebo) are: somnolence, dizziness, fatigue, nausea, and exacerbated insomnia. (6.1)

To report SUSPECTED ADVERSE REACTIONS, contact Takeda Pharmaceuticals America, Inc. at 1-877-TAKEDA-7 (1-877-825-3327) or FDA at 1-800-FDA-1088 or www.fda.gov/medwatch.

7 DRUG INTERACTIONS

- Rifampin (strong CYP enzyme inducer): Decreases exposure to and effects of ramelteon. (7.1)
- Ketoconazole (strong CYP3A4 inhibitor): Increases AUC for ramelteon; administer with caution. (7.1)
- Fluconazole (strong CYP2C9 inhibitor): Increases systemic exposure of ramelteon; administer with caution. (7.1)
- Donepezil: Increases systemic exposure of ramelteon; patients should be closely monitored when ramelteon is coadministered with donepezil. (7.1)
- Doxepin: Increases systemic exposure of ramelteon; patients should be closely monitored when ramelteon is coadministered with doxepin. (7.1)
- Alcohol: Causes additive psychomotor impairment; should not be used in combination. (7.2)

8 USE IN SPECIFIC POPULATIONS

- Pediatric use: Safety and effectiveness not established. (8.4)
- Geriatric use: No overall differences in safety and efficacy between elderly and younger adult subjects. (8.5)
- Hepatic impairment: Is not recommended in patients with severe impairment; use with caution in moderate impairment. (8.8)

FULL PRESCRIBING INFORMATION

1 INDICATIONS AND USAGE

ROZEREM® is indicated for the treatment of insomnia characterized by difficulty with sleep onset.

The clinical trials performed in support of efficacy were up to six months in duration. The final formal assessments of sleep latency were performed after two days of treatment during the crossover study (elderly only), at five weeks in the six week studies (adults and elderly), and at the end of the six month study (adults and elderly) [see Clinical Studies (14)].

2 DOSAGE AND ADMINISTRATION

2.1 Dosage in Adults

The recommended dose of ROZEREM is 8 mg taken within 30 minutes of going to bed. It is recommended that ROZEREM not be taken with or immediately after a high-fat meal.

The total ROZEREM dose should not exceed 8 mg per day.

2.2 Dosing in Patients with Hepatic Impairment

ROZEREM is not recommended in patients with severe hepatic impairment. ROZEREM should be used with caution in patients with moderate hepatic impairment [see Warnings and Precautions (5.6), Clinical Pharmacology (12.4)].

2.3 Administration with Other Medications

ROZEREM should not be used in combination with fluvoxamine. ROZEREM should be used with caution in patients taking other CYP1A2 inhibiting drugs [see Drug Interactions (7), Clinical Pharmacology (12.5)].

3 DOSAGE FORMS AND STRENGTHS

ROZEREM is available in an 8 mg strength tablet for oral administration.

ROZEREM 8 mg tablets are round, pale orange-yellow, film-coated, with "TAK" and "RAM-8" printed on one side.

4 CONTRAINDICATIONS

Patients who develop angioedema after treatment with ROZEREM should not be rechallenged with the drug.

Patients should not take ROZEREM in conjunction with fluvoxamine [see Drug Interactions (7)].

5 WARNINGS AND PRECAUTIONS

5.1 Severe Anaphylactic and Anaphylactoid Reactions

Rare cases of angioedema involving the tongue, glottis or larynx have been reported in patients after taking the first or subsequent doses of ROZEREM. Some patients have had additional symptoms such as dyspnea, throat closing, or nausea and vomiting that suggest anaphylaxis. Some patients have required medical therapy in the emergency department. If angioedema involves the tongue, glottis or larynx, airway obstruction may occur and be fatal. Patients who develop angioedema after treatment with ROZEREM should not be rechallenged with the drug.

5.2 Need to Evaluate for Comorbid Diagnoses

Since sleep disturbances may be the presenting manifestation of a physical and/or psychiatric disorder, symptomatic treatment of insomnia should be initiated only after a careful evaluation of the patient. The failure of insomnia to remit after 7 to 10 days of treatment may indicate the presence of a primary psychiatric and/or medical illness that should be evaluated. Worsening of insomnia, or the emergence of new cognitive or behavioral abnormalities, may be the result of an unrecognized underlying psychiatric or physical disorder and requires further evaluation of the patient. Exacerbation of insomnia and emergence of cognitive and behavioral abnormalities were seen with ROZEREM during the clinical development program.

5.3 Abnormal Thinking and Behavioral Changes

A variety of cognitive and behavior changes have been reported to occur in association with the use of hypnotics. In primarily depressed patients, worsening of depression (including suicidal ideation and completed suicides) has been reported in association with the use of hypnotics.

Hallucinations, as well as behavioral changes such as bizarre behavior, agitation and mania have been reported with ROZEREM use. Amnesia, anxiety and other neuro-psychiatric symptoms may also occur unpredictably.

Complex behaviors such as "sleep-driving" (i.e., driving while not fully awake after ingestion of a hypnotic) and other complex behaviors (e.g., preparing and eating food, making phone calls, or having sex), with amnesia for the event, have been reported in association with hypnotic use. The use of alcohol and other CNS depressants may increase the risk of such behaviors. These events can occur in hypnotic-naive as well as in hypnotic-experienced persons. Complex behaviors have been reported with the use of ROZEREM. Discontinuation of ROZEREM should be strongly considered for patients who report any complex sleep behavior.

5.4 CNS Effects

Patients should avoid engaging in hazardous activities that require concentration (such as operating a motor vehicle or heavy machinery) after taking ROZEREM.

After taking ROZEREM, patients should confine their activities to those necessary to prepare for bed.

Patients should be advised not to consume alcohol in combination with ROZEREM as alcohol and ROZEREM may have additive effects when used in conjunction.

5.5 Reproductive Effects

ROZEREM has been associated with an effect on reproductive hormones in adults, e.g., decreased testosterone levels and increased prolactin levels. It is not known what effect chronic or even chronic intermittent use of ROZEREM may have on the reproductive axis in developing humans [see Clinical Trials (14.3)].

5.6 Use in Patients with Concomitant Illness

ROZEREM has not been studied in subjects with severe sleep apnea and is not recommended for use in this population [see Use in Specific Populations (8.7)].

ROZEREM should not be used by patients with severe hepatic impairment [see Clinical Pharmacology (12.4)].

5.7 Laboratory Tests

Monitoring

No standard monitoring is required.

For patients presenting with unexplained amenorrhea, galactorrhea, decreased libido, or problems with fertility, assessment of prolactin levels and testosterone levels should be considered as appropriate.

Interference with Laboratory Tests

ROZEREM is not known to interfere with commonly used clinical laboratory tests. In addition, in vitro data indicate that ramelteon does not cause false-positive results for benzodiazepines, opiates, barbiturates, cocaine, cannabinoids, or amphetamines in two standard urine drug screening methods in vitro.

6 ADVERSE REACTIONS

The following serious adverse reactions are discussed in greater detail in other sections:

- Severe anaphylactic and anaphylactoid reactions [see Warnings and Precautions (5.1)]
- Abnormal thinking, behavior changes, and complex behaviors [see Warnings and Precautions (5.3)]
- CNS effects [see Warnings and Precautions (5.4)]

6.1 Clinical Trials Experience

Adverse Reactions Resulting in Discontinuation of Treatment

The data described in this section reflect exposure to ROZEREM in 5373 subjects, including 722 exposed for six months or longer, and 448 subjects for one year.

Six percent of the 5373 individual subjects exposed to ROZEREM in clinical studies discontinued treatment owing to an adverse event, compared with 2% of the 2279 subjects receiving placebo. The most frequent adverse events leading to discontinuation in subjects receiving ROZEREM were somnolence, dizziness, nausea, fatigue, headache, and insomnia; all of which occurred in 1% of the patients or less.

ROZEREM Most Commonly Observed Adverse Events

Table 1 displays the incidence of adverse events reported by the 2861 patients with chronic insomnia who participated in placebo-controlled trials of ROZEREM.

Because clinical trials are conducted under widely varying conditions, adverse reaction rates observed in the clinical trials of a drug cannot be directly compared to rates in clinical trials of other drugs, and may not reflect the rates observed in practice. The adverse reaction information from clinical trials does, however, provide a basis for identifying the adverse events that appear to be related to drug use and for approximating rates.

Table 1. Incidence (% of subjects) of Treatment-Emergent Adverse Events
MedDRA Preferred Term | Placebo (n=1456) | Ramelteon 8 mg (n=1405)
Somnolence | 2% | 3%
Fatigue | 2% | 3%
Dizziness | 3% | 4%
Nausea | 2% | 3%
Insomnia exacerbated | 2% | 3%

7 DRUG INTERACTIONS

7.1 Effects of Other Drugs on ROZEREM

Fluvoxamine (strong CYP1A2 inhibitor)

AUC0-inf for ramelteon increased approximately 190-fold, and the Cmax increased approximately 70-fold upon coadministration of fluvoxamine and ROZEREM, compared to ROZEREM administered alone. ROZEREM should not be used in combination with fluvoxamine [see Contraindications (4), Clinical Pharmacology (12.5)]. Other less strong CYP1A2 inhibitors have not been adequately studied. ROZEREM should be administered with caution to patients taking less strong CYP1A2 inhibitors.

Rifampin (strong CYP enzyme inducer)

Administration of multiple doses of rifampin resulted in a mean decrease of approximately 80% in total exposure to ramelteon and metabolite M-II. Efficacy may be reduced when ROZEREM is used in combination with strong CYP enzyme inducers such as rifampin [see Clinical Pharmacology (12.5)].

Ketoconazole (strong CYP3A4 inhibitor)

The AUC0-inf and Cmax of ramelteon increased by approximately 84% and 36% upon coadministration of ketoconazole with ROZEREM. ROZEREM should be administered with caution in subjects taking strong CYP3A4 inhibitors such as ketoconazole [see Clinical Pharmacology (12.5)].

Fluconazole (strong CYP2C9 inhibitor)

The AUC0-inf and Cmax of ramelteon was increased by approximately 150% when ROZEREM was coadministered with fluconazole. ROZEREM should be administered with caution in subjects taking strong CYP2C9 inhibitors such as fluconazole [see Clinical Pharmacology (12.5)].

Donepezil

The AUC0-inf and Cmax of ramelteon increased by approximately 100% and 87%, respectively upon coadministration of donepezil with ROZEREM. Patients should be closely monitored when ROZEREM is coadministered with donepezil [see Clinical Pharmacology (12.5)].

Doxepin

The AUC0-inf and Cmax of ramelteon increased by approximately 66% and 69%, respectively, upon coadministration of doxepin with ROZEREM. Patients should be closely monitored when ROZEREM is coadministered with doxepin [see Clinical Pharmacology (12.5)].

7.2 Effect of Alcohol on ROZEREM

Alcohol by itself impairs performance and can cause sleepiness. Since the intended effect of ROZEREM is to promote sleep, patients should be cautioned not to consume alcohol when using ROZEREM [see Clinical Pharmacology (12.5)]. Use of the products in combination may have an additive effect.

7.3 Drug/Laboratory Test Interactions

ROZEREM is not known to interfere with commonly used clinical laboratory tests. In addition, in vitro data indicate that ramelteon does not cause false-positive results for benzodiazepines, opiates, barbiturates, cocaine, cannabinoids, or amphetamines in two standard urine drug screening methods in vitro.

8 USE IN SPECIFIC POPULATIONS

8.1 Pregnancy

Risk Summary

Available data from postmarketing reports with ROZEREM use in pregnant women have not identified a drug-associated risk of major birth defects, miscarriage, or adverse maternal or fetal outcomes. In animal studies, ramelteon produced evidence of developmental toxicity, including teratogenic effects, in rats at doses greater than 36 times the recommended human dose (RHD) of 8 mg/day based on body surface area (mg/m^2) (see Data).

The estimated background risk of major birth defects and miscarriage for the indicated population is unknown. All pregnancies have a background risk of birth defect, loss, or other adverse outcomes. In the U.S. general population, the estimated background risk of major birth defects and miscarriage in clinically recognized pregnancies is 2 - 4% and 15 - 20%, respectively.

Data

Animal Data

Oral administration of ramelteon (10, 40, 150, or 600 mg/kg/day) to pregnant rats during the period of organogenesis was associated with increased incidences of fetal structural abnormalities (malformations and variations) at doses greater than 40 mg/kg/day. The no-effect dose is approximately 50 times the RHD based on mg/m^2. Treatment of pregnant rabbits during the period of organogenesis produced no evidence of embryo-fetal toxicity at oral doses of up to 300 mg/kg/day (or up to 720 times the RHD based on mg/m^2).

When rats were orally administered ramelteon (30, 100, or 300 mg/kg/day) throughout gestation and lactation, growth retardation, developmental delay, and behavioral changes were observed in the offspring at doses greater than 30 mg/kg/day. The no-effect dose is 36 times the RHD based on mg/m^2. Increased incidences of malformation and death among offspring were seen at the highest dose.

8.2 Lactation

Risk Summary

There are no data regarding the presence of ramelteon or its metabolites in human milk, the effects on the breastfed infant, or the effects on milk production. Ramelteon and/or its metabolites are present in rat milk. When a drug is present in animal milk, it is likely that the drug will be present in human milk. Because of the mechanism of action of ramelteon, there is a potential risk for somnolence in a breastfed infant (see Clinical Considerations). The developmental and health benefits of breastfeeding should be considered along with the mother's clinical need for ROZEREM and any potential adverse effects on the breastfed infant from ROZEREM or from the underlying maternal condition.

Clinical Considerations

Infants exposed to ROZEREM through breastmilk should be monitored for somnolence and feeding problems. A lactating woman may consider interrupting breastfeeding and pumping and discarding breast milk during treatment and for 25 hours (approximately 5 elimination half-lives) after ROZEREM administration in order to minimize drug exposure to a breastfed infant.

8.4 Pediatric Use

Safety and effectiveness of ROZEREM in pediatric patients have not been established. Further study is needed prior to determining that this product may be used safely in prepubescent and pubescent patients.

8.5 Geriatric Use

A total of 654 subjects in double-blind, placebo-controlled, efficacy trials who received ROZEREM were at least 65 years of age; of these, 199 were 75 years of age or older. No overall differences in safety or efficacy were observed between elderly and younger adult subjects.

A double-blind, randomized, placebo-controlled study in elderly subjects with insomnia (n=33) evaluated the effect of a single dose of ROZEREM on balance, mobility, and memory functions after middle of the night awakening. There is no information on the effect of multiple dosing. Night time dosing of ROZEREM 8 mg did not impair middle of the night balance, mobility, or memory functions relative to placebo. The effects on night balance in the elderly cannot be definitively known from this study.

8.6 Chronic Obstructive Pulmonary Disease

The respiratory depressant effect of ROZEREM was evaluated in a crossover design study of subjects (n=26) with mild to moderate COPD after administering a single 16 mg dose or placebo, and in a separate study (n=25), the effects of ROZEREM on respiratory parameters were evaluated after administering an 8 mg dose or placebo in a crossover design to patients with moderate to severe COPD, defined as patients who had forced expiratory volume at one second (FEV1)/forced vital capacity ratio of <70%, and a FEV1 <80% of predicted with <12% reversibility to albuterol. Treatment with a single dose of ROZEREM has no demonstrable respiratory depressant effects in subjects with mild to severe COPD, as measured by arterial O2 saturation (SaO2). There is no available information on the respiratory effects of multiple doses of ROZEREM in patients with COPD. The respiratory depressant effects in patients with COPD cannot be definitively known from this study.

8.7 Sleep Apnea

The effects of ROZEREM were evaluated after administering a 16 mg dose or placebo in a crossover design to subjects (n=26) with mild to moderate obstructive sleep apnea. Treatment with ROZEREM 16 mg for one night showed no difference compared with placebo on the Apnea/Hypopnea Index (the primary outcome variable), apnea index, hypopnea index, central apnea index, mixed apnea index, and obstructive apnea index. Treatment with a single dose of ROZEREM does not exacerbate mild to moderate obstructive sleep apnea. There is no available information on the respiratory effects of multiple doses of ROZEREM in patients with sleep apnea. The effects on exacerbation in patients with mild to moderate sleep apnea cannot be definitively known from this study.

ROZEREM has not been studied in subjects with severe obstructive sleep apnea; use of ROZEREM is not recommended in such patients.

8.8 Hepatic Impairment

Exposure to ROZEREM was increased by four-fold in subjects with mild hepatic impairment and by more than ten-fold in subjects with moderate hepatic impairment. ROZEREM should be used with caution in patients with moderate hepatic impairment [see Clinical Pharmacology (12.4)]. ROZEREM is not recommended in patients with severe hepatic impairment.

8.9 Renal Impairment

No effects on Cmax and AUC0-t of parent drug or M-II were seen. No adjustment of ROZEREM dosage is required in patients with renal impairment [see Clinical Pharmacology (12.4)].

9 DRUG ABUSE AND DEPENDENCE

ROZEREM is not a controlled substance.

Discontinuation of ramelteon in animals or in humans after chronic administration did not produce withdrawal signs. Ramelteon does not appear to produce physical dependence.

Human Data

A laboratory abuse potential study was performed with ROZEREM [see Clinical Studies (14.2)].

Animal Data

Ramelteon did not produce any signals from animal behavioral studies indicating that the drug produces rewarding effects. Monkeys did not self-administer ramelteon and the drug did not induce a conditioned place preference in rats. There was no generalization between ramelteon and midazolam. Ramelteon did not affect rotorod performance, an indicator of disruption of motor function, and it did not potentiate the ability of diazepam to interfere with rotorod performance.

10 OVERDOSAGE

General symptomatic and supportive measures should be used, along with immediate gastric lavage where appropriate. Intravenous fluids should be administered as needed. As in all cases of drug overdose, respiration, pulse, blood pressure, and other appropriate vital signs should be monitored, and general supportive measures employed.

Hemodialysis does not effectively reduce exposure to ROZEREM. Therefore, the use of dialysis in the treatment of overdosage is not appropriate.

Poison Control Center

As with the management of all overdosage, the possibility of multiple drug ingestion should be considered. Contact a poison control center for current information on the management of overdosage.

11 DESCRIPTION

ROZEREM (ramelteon) is an orally active hypnotic chemically designated as (S)-N-[2-(1,6,7,8-tetrahydro-2H-indeno-[5,4-b]furan-8-yl)ethyl]propionamide and containing one chiral center. The compound is produced as the (S)-enantiomer, with an empirical formula of C16H21NO2, molecular weight of 259.34, and the following chemical structure:

Ramelteon is freely soluble in organic solvents, such as methanol, ethanol, and dimethyl sulfoxide; soluble in 1-octanol and acetonitrile; and very slightly soluble in water and in aqueous buffers from pH 3 to pH 11.

Each ROZEREM tablet includes the following inactive ingredients: lactose monohydrate, starch, hydroxypropyl cellulose, magnesium stearate, hypromellose, copovidone, titanium dioxide, yellow ferric oxide, polyethylene glycol 8000, and ink containing shellac and synthetic iron oxide black.

12 CLINICAL PHARMACOLOGY

12.1 Mechanism of Action

Ramelteon is a melatonin receptor agonist with both high affinity for melatonin MT1 and MT2 receptors and relative selectivity over the MT3 receptor.

The activity of ramelteon at the MT1 and MT2 receptors is believed to contribute to its sleep-promoting properties, as these receptors, acted upon by endogenous melatonin, are thought to be involved in the maintenance of the circadian rhythm underlying the normal sleep-wake cycle.

Ramelteon has no appreciable affinity for the GABA receptor complex or for receptors that bind neuropeptides, cytokines, serotonin, dopamine, noradrenaline, acetylcholine, and opiates. Ramelteon also does not interfere with the activity of a number of selected enzymes in a standard panel.

The major metabolite of ramelteon, M-II, is pharmacologically active and has approximately one tenth and one fifth the binding affinity of the parent molecule for the human MT1 and MT2 receptors, respectively. However, M-II circulates at higher concentrations than the parent producing 20- to 100-fold greater mean systemic exposure when compared to ramelteon. Similar to ramelteon, M-II does not interfere with the activity of a number of endogenous enzymes.

All other known metabolites of ramelteon are inactive.

12.3 Pharmacokinetics

The pharmacokinetic profile of ROZEREM has been evaluated in healthy subjects as well as in subjects with hepatic or renal impairment. When administered orally to humans in doses ranging from 4 to 64 mg, ramelteon undergoes rapid, high first-pass metabolism, and exhibits linear pharmacokinetics. Maximal serum concentration (Cmax) and area under the concentration-time curve (AUC) data show substantial intersubject variability, consistent with the high first-pass effect; the coefficient of variation for these values is approximately 100%. Several metabolites have been identified in human serum and urine.

Absorption

Ramelteon is absorbed rapidly, with median peak concentrations occurring at approximately 0.75 hour (range, 0.5 to 1.5 hours) after fasted oral administration. Although the total absorption of ramelteon is at least 84%, the absolute oral bioavailability is only 1.8% due to extensive first-pass metabolism.

Distribution

In vitro protein binding of ramelteon is approximately 82% in human serum, independent of concentration. Binding to albumin accounts for most of that binding, since 70% of the drug is bound in human serum albumin. Ramelteon is not distributed selectively to red blood cells.

Ramelteon has a mean volume of distribution after intravenous administration of 73.6 L, suggesting substantial tissue distribution.

Metabolism

Metabolism of ramelteon consists primarily of oxidation to hydroxyl and carbonyl derivatives, with secondary metabolism producing glucuronide conjugates. CYP1A2 is the major isozyme involved in the hepatic metabolism of ramelteon; the CYP2C subfamily and CYP3A4 isozymes are also involved to a minor degree.

The rank order of the principal metabolites by prevalence in human serum is M-II, M-IV, M-I, and M-III. These metabolites are formed rapidly and exhibit a monophasic decline and rapid elimination. The overall mean systemic exposure of M-II is approximately 20- to 100-fold higher than parent drug.

Elimination

Following oral administration of radiolabeled ramelteon, 84% of total radioactivity was excreted in urine and approximately 4% in feces, resulting in a mean recovery of 88%. Less than 0.1% of the dose was excreted in urine and feces as the parent compound. Elimination was essentially complete by 96 hours postdose.

Repeated once daily dosing with ROZEREM does not result in significant accumulation owing to the short elimination half-life of ramelteon (on average, approximately one to 2.6 hours).

The half-life of M-II is two to five hours and independent of dose. Serum concentrations of the parent drug and its metabolites in humans are at or below the lower limits of quantitation within 24 hours.

Effect of Food

When administered with a high-fat meal, the AUC0-inf for a single 16 mg dose of ROZEREM was 31% higher and the Cmax was 22% lower than when given in a fasted state. Median Tmax was delayed by approximately 45 minutes when ROZEREM was administered with food. Effects of food on the AUC values for M-II were similar. It is therefore recommended that ROZEREM not be taken with or immediately after a high-fat meal [see Dosage and Administration (2.1)].

12.4 Pharmacokinetics in Special Populations

Age

In a group of 24 elderly subjects aged 63 to 79 years administered a single ROZEREM 16 mg dose, the mean Cmax and AUC0-inf values were 11.6 ng/mL (SD, 13.8) and 18.7 ng∙hr/mL (SD, 19.4), respectively. The elimination half-life was 2.6 hours (SD, 1.1). Compared with younger adults, the total exposure (AUC0-inf) and Cmax of ramelteon were 97 and 86% higher, respectively, in elderly subjects. The AUC0-inf and Cmax of M-II were increased by 30 and 13%, respectively, in elderly subjects.

Gender

There are no clinically meaningful gender-related differences in the pharmacokinetics of ROZEREM or its metabolites.

Hepatic Impairment

Exposure to ROZEREM was increased almost four-fold in subjects with mild hepatic impairment after seven days of dosing with 16 mg/day; exposure was further increased (more than ten-fold) in subjects with moderate hepatic impairment. Exposure to M-II was only marginally increased in mildly and moderately impaired subjects relative to healthy matched controls. The pharmacokinetics of ROZEREM have not been evaluated in subjects with severe hepatic impairment (Child-Pugh Class C). ROZEREM should be used with caution in patients with moderate hepatic impairment [see Warnings and Precautions (5.6)].

Renal Impairment

The pharmacokinetic characteristics of ROZEREM were studied after administering a 16 mg dose to subjects with mild, moderate, or severe renal impairment based on predose creatinine clearance (53 to 95, 35 to 49, or 15 to 30 mL/min/1.73 m^2, respectively), and in subjects who required chronic hemodialysis. Wide intersubject variability was seen in ROZEREM exposure parameters. However, no effects on Cmax or AUC0-t of parent drug or M-II were seen in any of the treatment groups; the incidence of adverse events was similar across groups. These results are consistent with the negligible renal clearance of ramelteon, which is principally eliminated via hepatic metabolism. No adjustment of ROZEREM dosage is required in patients with renal impairment, including patients with severe renal impairment (creatinine clearance of ≤30 mL/min/1.73 m^2) and patients who require chronic hemodialysis.

12.5 Drug-Drug Interactions

ROZEREM has a highly variable intersubject pharmacokinetic profile (approximately 100% coefficient of variation in Cmax and AUC). As noted above, CYP1A2 is the major isozyme involved in the metabolism of ROZEREM; the CYP2C subfamily and CYP3A4 isozymes are also involved to a minor degree.

Effects of Other Drugs on ROZEREM Metabolism

Fluvoxamine (strong CYP1A2 inhibitor)

When fluvoxamine 100 mg twice daily was administered for three days prior to single-dose coadministration of ROZEREM 16 mg and fluvoxamine, the AUC0-inf for ramelteon increased approximately 190-fold, and the Cmax increased approximately 70-fold, compared to ROZEREM administered alone. ROZEREM should not be used in combination with fluvoxamine. Other less strong CYP1A2 inhibitors have not been adequately studied. ROZEREM should be administered with caution to patients taking less strong CYP1A2 inhibitors [see Contraindications (4), Drug Interactions (7)].

Rifampin (strong CYP enzyme inducer)

Administration of rifampin 600 mg once daily for 11 days resulted in a mean decrease of approximately 80% (40 to 90%) in total exposure to ramelteon and metabolite M-II, (both AUC0-inf and Cmax) after a single 32 mg dose of ROZEREM. Efficacy may be reduced when ROZEREM is used in combination with strong CYP enzyme inducers such as rifampin [see Drug Interactions (7)].

Ketoconazole (strong CYP3A4 inhibitor)

The AUC0-inf and Cmax of ramelteon increased by approximately 84% and 36%, respectively, when a single 16 mg dose of ROZEREM was administered on the fourth day of ketoconazole 200 mg twice daily administration, compared to administration of ROZEREM alone. Similar increases were seen in M-II pharmacokinetic variables. ROZEREM should be administered with caution in subjects taking strong CYP3A4 inhibitors such as ketoconazole [see Drug Interactions (7)].

Fluconazole (strong CYP2C9 inhibitor)

The total and peak systemic exposure (AUC0-inf and Cmax) of ramelteon after a single 16 mg dose of ROZEREM was increased by approximately 150% when administered with fluconazole. Similar increases were also seen in M-II exposure. ROZEREM should be administered with caution in subjects taking strong CYP2C9 inhibitors such as fluconazole [see Drug Interactions (7)].

Donepezil

Administration of donepezil 10 mg once daily for 26 days resulted in a mean increase of approximately 100% in overall exposure to ramelteon, (AUC0-inf) and a mean increase of approximately 87% in maximum exposure to ramelteon (Cmax) after a single 8 mg dose of ROZEREM. No change was seen in M-II exposure. Patients should be closely monitored when ROZEREM is coadministered with donepezil [see Drug Interactions (7)].

Doxepin

Administration of doxepin 10 mg once daily for 23 days resulted in a mean increase of approximately 66% in overall exposure to ramelteon, (AUC0-inf) and a mean increase of approximately 69% in maximum exposure to ramelteon (Cmax) after a single 8 mg dose of ROZEREM. No change was seen in M-II exposure. Patients should be closely monitored when ROZEREM is coadministered with doxepin [see Drug Interactions (7)].

Interaction studies of concomitant administration of ROZEREM with fluoxetine (CYP2D6 inhibitor), omeprazole (CYP1A2 inducer/CYP2C19 inhibitor), theophylline (CYP1A2 substrate), dextromethorphan (CYP2D6 substrate), sertraline, venlafaxine, escitalopram, gabapentin, and zolpidem did not produce clinically meaningful changes in either peak or total exposures to ramelteon or the M-II metabolite.

Effects of ROZEREM on Metabolism of Other Drugs

Zolpidem

Administration of ramelteon 8 mg once daily for 11 days resulted in an increase in median Tmax of zolpidem by approximately 20 minutes and exposure to zolpidem (both AUC0-inf and Cmax) was unchanged after a single 10 mg dose of zolpidem. Ordinarily zolpidem should not be given in a patient taking ROZEREM.

Concomitant administration of ROZEREM with omeprazole (CYP2C19 substrate), dextromethorphan (CYP2D6 substrate), midazolam (CYP3A4 substrate), theophylline (CYP1A2 substrate), digoxin (p-glycoprotein substrate), warfarin (CYP2C9 [S]/CYP1A2 [R] substrate), venlafaxine, fluvoxamine, donepezil, doxepin, sertraline, escitalopram, and gabapentin did not produce clinically meaningful changes in peak and total exposures to these drugs.

Effect of Alcohol on ROZEREM

With single-dose, daytime coadministration of ROZEREM 32 mg and alcohol (0.6 g/kg), there were no clinically meaningful or statistically significant effects on peak or total exposure to ROZEREM. However, an additive effect was seen on some measures of psychomotor performance (i.e., the Digit Symbol Substitution Test, the Psychomotor Vigilance Task Test, and a Visual Analog Scale of Sedation) at some postdose time points. No additive effect was seen on the Delayed Word Recognition Test. Because alcohol by itself impairs performance, and the intended effect of ROZEREM is to promote sleep, patients should be cautioned not to consume alcohol when using ROZEREM.

13 NONCLINICAL TOXICOLOGY

13.1 Carcinogenesis, Mutagenesis, Impairment of Fertility

Carcinogenesis

Ramelteon was administered to mice and rats at oral doses of 0, 30, 100, 300, or 1000 mg/kg/day (mice) and 0, 15, 60, 250, or 1000 mg/kg/day (rats). Mice and rats were dosed for two years, except at the high dose (94 weeks for male and female mice and female rats). In mice, dose-related increases in the incidence of hepatic tumors (adenomas, carcinomas, hepatoblastomas) were observed in males and females. The no-effect dose for hepatic tumors in mice (30 mg/kg/day) is approximately 20 times the recommended human dose (RHD) of 8 mg/day based on body surface area (mg/m^2).

In rats, the incidence of hepatic adenoma and benign Leydig cell tumors of the testis was increased in males at doses ≥250 mg/kg/day. In females, the incidence of hepatic adenoma was increased at doses ≥60 mg/kg/day. The incidence of hepatic carcinoma was increased in males and female rats at 1000 mg/kg/day. The no-effect dose for tumors in rats (15 mg/kg/day) is approximately 20 times the RHD based on mg/m^2.

Mutagenesis

Ramelteon was not genotoxic in the in vitro bacterial reverse mutation (Ames) assay, the in vitro mouse lymphoma TK+/- assay, and in in vivo oral micronucleus assays in mouse and rat. Ramelteon was clastogenic in the in vitro chromosomal aberration assay in Chinese hamster lung cells.

The M-II metabolite was not tested for genotoxicity. However, it was present in the test medium of the parent drug at concentrations higher than those of the parent.

Impairment of Fertility

When ramelteon (doses of 6 to 600 mg/kg/day) was administered orally to male and female rats prior to and during mating and early gestation, alterations in estrus cyclicity and decreased numbers of corpora lutea, implantations, and live embryos were observed at doses greater than 20 mg/kg/day. The no-effect dose is approximately 24 times the RHD of 8 mg/day based on mg/m^2. Oral administration of ramelteon (up to 600 mg/kg/day) to male rats had no effects on sperm quality or reproductive performance.

14 CLINICAL STUDIES

14.1 Controlled Clinical Trials

Chronic Insomnia

Three randomized, double-blind trials in subjects with chronic insomnia employing polysomnography (PSG) were provided as objective support of ROZEREM'S effectiveness in sleep initiation.

One study enrolled younger adults (aged 18 to 64 years, inclusive) with chronic insomnia and employed a parallel design in which the subjects received a single, nightly dose of ROZEREM (8 or 16 mg) or matching placebo for 35 days. PSG was performed on the first two nights in each of Weeks 1, 3, and 5 of treatment. ROZEREM reduced the average latency to persistent sleep at each of the time points when compared to placebo. The 16 mg dose conferred no additional benefit for sleep initiation.

The second study employing PSG was a three-period crossover trial performed in subjects aged 65 years and older with a history of chronic insomnia. Subjects received ROZEREM (4 or 8 mg) or placebo and underwent PSG assessment in a sleep laboratory for two consecutive nights in each of the three study periods. Both doses of ROZEREM reduced latency to persistent sleep when compared to placebo.

The third study evaluated long-term efficacy and safety in adults with chronic insomnia. Subjects received a single, nightly dose of ROZEREM 8 mg or matching placebo for six months. PSG was performed on the first two nights of Week 1 and Months 1, 3, 5, and 6. ROZEREM reduced sleep latency at each time point when compared to placebo. In this study, when the PSG results from nights 1 and 2 of Month 7 were compared to the results from nights 22 and 23 of Month 6, there was a statistically significant increase in LPS of 33% (9.5 minutes) in the ramelteon group. There was no increase in LPS in the placebo group when the same time periods were compared.

A randomized, double-blind, parallel group study was conducted in outpatients aged 65 years and older with chronic insomnia and employed subjective measures of efficacy (sleep diaries). Subjects received ROZEREM (4 or 8 mg) or placebo for 35 nights. ROZEREM reduced patient-reported sleep latency compared to placebo. A similarly designed study performed in younger adults (aged 18 to 64 years) using 8 and 16 mg of ramelteon did not replicate this finding of reduced patient-reported sleep latency compared to placebo.

While the 16 mg dose was evaluated as a potential treatment for adults, it was shown to confer no additional benefit for sleep initiation and was associated with higher incidences of fatigue, headache and next-day somnolence.

Transient Insomnia

In a randomized, double-blind, parallel-group trial using a first-night-effect model, healthy adults received placebo or ROZEREM before spending one night in a sleep laboratory and being evaluated with PSG. ROZEREM demonstrated a decrease in mean latency to persistent sleep as compared to placebo.

14.2 Studies Pertinent to Safety Concerns for Sleep-Promoting Drugs

Results from Human Laboratory Abuse Liability Studies

A human laboratory abuse potential study was performed in 14 subjects with a history of sedative/hypnotic or anxiolytic drug abuse. Subjects received single oral doses of ROZEREM (16, 80, or 160 mg), triazolam (0.25, 0.50, or 0.75 mg) or placebo. All subjects received each of the seven treatments separated by a wash-out period and underwent multiple standard tests of abuse potential. No differences in subjective responses indicative of abuse potential were found between ROZEREM and placebo at doses up to 20 times the recommended therapeutic dose. The positive control drug, triazolam, consistently showed a dose-response effect on these subjective measures, as demonstrated by the differences from placebo in peak effect and overall 24 hour effect.

Residual Pharmacological Effect in Insomnia Trials

In order to evaluate potential next-day residual effects, the following scales were used: a Memory Recall Test, a Word List Memory Test, a Visual Analog Mood and Feeling Scale, the Digit-Symbol Substitution Test, and a post sleep questionnaire to assess alertness and ability to concentrate. There was no evidence of next-day residual effect seen after two nights of ramelteon use during the crossover studies.

In a 35 night, double-blind, placebo-controlled, parallel-group study in adults with chronic insomnia, measures of residual effects were performed at three time points. Overall, the magnitudes of any observed differences were small. At Week 1, patients who received 8 mg of ROZEREM had a mean VAS score (46 mm on a 100 mm scale) indicating more fatigue in comparison to patients who received placebo (42 mm). At Week 3, patients who received 8 mg of ROZEREM had a lower mean score for immediate recall (7.5 out of 16 words) compared to patients who received placebo (8.2 words); and the patients treated with ROZEREM had a mean VAS score indicating more sluggishness (27 mm on a 100 mm VAS) in comparison to the placebo-treated patients (22 mm). Patients who received ROZEREM did not have next-morning residual effects that were different from placebo at Week 5.

Rebound Insomnia/Withdrawal

Potential rebound insomnia and withdrawal effects were assessed in four studies in which subjects received ROZEREM or placebo for up to six months; three were 35 day studies, one was a six month study. These studies included a total of 2533 subjects, of whom 854 were elderly.

Tyrer Benzodiazepine Withdrawal Symptom Questionnaire (BWSQ)

The BWSQ is a self-report questionnaire that solicits specific information on 20 symptoms commonly experienced during withdrawal from benzodiazepine receptor agonists; ROZEREM is not a benzodiazepine receptor agonist.

In two of the three 35 day insomnia studies, the questionnaire was administered one week after completion of treatment; in the third study, the questionnaire was administered on Days 1 and 2 after completion. In all three of the 35 day studies, subjects receiving ROZEREM 4, 8, or 16 mg daily reported BWSQ scores similar to those of subjects receiving placebo.

In the six month study, there was no evidence of withdrawal from the 8 mg dose as measured by the BWSQ.

Rebound Insomnia

Rebound insomnia was assessed in the 35 day studies by measuring sleep latency after abrupt treatment discontinuation. One of these studies employed PSG in younger adult subjects receiving ROZEREM 8 or 16 mg; the other two studies employed subjective measures of sleep-onset insomnia in elderly subjects receiving ROZEREM 4 or 8 mg, and in younger adult subjects receiving ROZEREM 8 or 16 mg. There was no evidence that ROZEREM caused rebound insomnia during the posttreatment period.

14.3 Studies to Evaluate Effects on Endocrine Function

Two controlled studies evaluated the effects of ROZEREM on endocrine function.

In the first trial, ROZEREM 16 mg once daily or placebo was administered to 99 healthy volunteer subjects for four weeks. This study evaluated the thyroid axis, adrenal axis and reproductive axis. No clinically significant endocrinopathies were demonstrated in this study. However, the study was limited in its ability to detect such abnormalities due to its limited duration.

In the second trial, ROZEREM 16 mg once daily or placebo was administered to 122 subjects with chronic insomnia for six months. This study evaluated the thyroid axis, adrenal axis and reproductive axis. There were no significant abnormalities seen in either the thyroid or the adrenal axes. Abnormalities were, however, noted within the reproductive axis. Overall, the mean serum prolactin level change from baseline was 4.9 mcg/L (34% increase) for women in the ROZEREM group compared with -0.6 mcg/L (4% decrease) for women in the placebo group (p=0.003). No differences between active- and placebo-treated groups occurred among men. Thirty two percent of all patients who were treated with ramelteon in this study (women and men) had prolactin levels that increased from normal baseline levels compared to 19% of patients who were treated with placebo. Subject-reported menstrual patterns were similar between the two treatment groups.

In a 12 month, open-label study in adult and elderly patients, there were two patients who were noted to have abnormal morning cortisol levels, and subsequent abnormal ACTH stimulation tests. A 29 year old female patient was diagnosed with a prolactinoma. The relationship of these events to ROZEREM therapy is not clear.

16 HOW SUPPLIED/STORAGE AND HANDLING

ROZEREM is available as round, pale orange-yellow, film-coated, 8 mg tablets, with "TAK" and "RAM-8" printed on one side, in the following quantities:

NDC 64764-805-30 | Bottles of 30
NDC 64764-805-10 | Bottles of 100
NDC 64764-805-50 | Bottles of 500

STORAGE AND HANDLING

Store at 25°C (77°F); excursions permitted to 15° to 30°C (59° to 86°F) [see USP Controlled Room Temperature]. Keep container tightly closed and protected from moisture and humidity.

17 PATIENT COUNSELING INFORMATION

Advise the patient to read the FDA-approved patient labeling (Medication Guide).

Severe Anaphylactic and Anaphylactoid Reactions

Inform patients that severe anaphylactic and anaphylactoid reactions have occurred with ramelteon. Describe the relevant signs/symptoms and advise seeking immediate medical attention if any such things occur.

Sleep-Driving and other Complex Behaviors

There have been reports of people getting out of bed after taking a sleep medication and driving their cars while not fully awake, often with no memory of the event. If a patient experiences such an episode, it should be reported to his or her doctor immediately, since "sleep-driving" can be dangerous. This behavior is more likely to occur when sleep medications are taken with alcohol or other central nervous system depressants. Other complex behaviors (e.g., preparing and eating food, making phone calls, or having sex) have been reported in patients who are not fully awake after taking a sleep medication. As with sleep-driving, patients usually do not remember these events.

Endocrine Effects

Patients should consult their healthcare providers if they experience one of the following: cessation of menses or galactorrhea in females, decreased libido, or problems with fertility. Describe the relevant signs/symptoms and advise seeking medical attention if any such things occur.

Administration Instructions

- Patients should be advised to take ROZEREM within 30 minutes prior to going to bed and should confine their activities to those necessary to prepare for bed.
- Patients should be advised that they should not take ROZEREM with or immediately after a high-fat meal.
- Do not break the tablet; it should be swallowed whole.

Lactation

Advise mothers using ROZEREM to monitor neonates for signs of somnolence and feeding problems. A lactating woman may consider pumping and discarding breast milk during treatment and for 25 hours after ROZEREM administration to minimize drug exposure to a breastfed infant [see Use in Specific Populations (8.2)].

MEDICATION GUIDE

ROZEREM® (rō-Zair-em)

(ramelteon)

Read the Medication Guide that comes with ROZEREM before you start taking it and each time you get a refill. There may be new information. This Medication Guide does not take the place of talking to your doctor about your medical condition or treatment.

What is the most important information I should know about ROZEREM?

ROZEREM may cause severe allergic reactions. Symptoms include swelling of the tongue or throat, trouble breathing, and nausea and vomiting. Get emergency medical help if you get these symptoms after taking ROZEREM.

After taking ROZEREM, you may get up out of bed while not being fully awake and do an activity that you do not know you are doing. The next morning, you may not remember that you did anything during the night. You have a higher chance for doing these activities if you drink alcohol or take other medicines that make you sleepy with ROZEREM. Activities may include:

- driving a car ("sleep-driving")
- making and eating food
- talking on the phone
- having sex
- sleep-walking

Call your doctor right away if you find out that you have done any of the above activities after taking ROZEREM.

Important:

1. Take ROZEREM exactly as prescribed
  - Do not take more ROZEREM than prescribed.
  - Take ROZEREM within 30 minutes of going to bed, not sooner.
2. Do not take ROZEREM if you:
  - drink alcohol
  - take other medicines that can make you sleepy. Talk to your doctor about all of your medicines. Your doctor will tell you if you can take ROZEREM with your other medicines
  - cannot get a full night's sleep

WHAT IS ROZEREM?

ROZEREM is a hypnotic (sleep) medicine. ROZEREM is used in adults for the treatment of the symptom of trouble falling asleep from insomnia.

ROZEREM is not for children.

Who should not take ROZEREM?

Do not take ROZEREM if you are allergic to anything in it. See the end of this Medication Guide for a complete list of ingredients in ROZEREM.

Do not take ROZEREM if you are currently taking Luvox (fluvoxamine).

ROZEREM may not be right for you. Before starting ROZEREM, tell your doctor about all of your health conditions, including if you:

- have a history of depression, mental illness, or suicidal thoughts
- have liver disease
- have a lung disease or breathing problems
- are pregnant, or planning to become pregnant
- are breastfeeding or plan to breastfeed. ROZEREM may cause somnolence in a breastfed infant. You may consider interrupting breastfeeding and pumping and discarding breastmilk during treatment and for 25 hours after administration of ROZEREM.

Tell your doctor about all of the medicines you take including prescription and nonprescription medicines, vitamins and herbal supplements. Medicines can interact with each other, sometimes causing serious side effects.

Do not take ROZEREM with:

- other medicines that can make you sleepy
- Luvox (fluvoxamine)

Know the medicines you take. Keep a list of your medicines with you to show your doctor and pharmacist each time you get a new medicine.

How should I take ROZEREM?

- Take ROZEREM exactly as prescribed. Do not take more ROZEREM than prescribed for you.
- Do not break the tablets. They should be swallowed whole.
- Take ROZEREM within 30 minutes of going to bed. After taking ROZEREM only do activities to get ready for bed.
- Do not take ROZEREM with or right after a meal.
- Do not take ROZEREM unless you are able to get a full night's sleep before you must be active again.
- Call your doctor if your insomnia worsens or is not better within 7 to 10 days. This may mean that there is another condition causing your sleep problems.
- If you take too much ROZEREM or overdose, call your doctor or poison control center right away, or get emergency treatment.

What are the possible side effects of ROZEREM?

Possible serious side effects of ROZEREM include:

- severe allergic reactions. Symptoms include swelling of the tongue or throat, trouble breathing, and nausea and vomiting. Get emergency medical help if you get these symptoms after taking ROZEREM.
- getting out of bed while not being fully awake and do an activity that you do not know you are doing. (See "What is the most important information I should know about ROZEREM?")
- abnormal thoughts and behavior. Symptoms include worsening of depression, suicidal thoughts or actions, nightmares, and hallucinations.
- hormone effects. ROZEREM can decrease testosterone levels and increase prolactin levels in the blood. Symptoms of low testosterone or high prolactin levels are:
  - decreased interest in sex
  - problems getting pregnant
  - irregular menstrual periods or no menstrual periods
  - leakage of milk from the nipples of a person who is not breastfeeding

Call your doctor right away if you have any of the above side effects or any other side effects that worry you while using ROZEREM. Call your doctor for medical advice about side effects. You may report side effects to the FDA at 1-800-FDA-1088.

The most common side effects of ROZEREM are:

- drowsiness
- tiredness
- dizziness
- You may still feel drowsy the next day after taking ROZEREM. Do not drive or do other dangerous activities after taking ROZEREM until you feel fully awake.

These are not all the side effects of ROZEREM. Ask your doctor or pharmacist for more information.

How should I Store ROZEREM?

- Store ROZEREM tablets at room temperature, 59° to 86° F (15° to 30°C). Keep the container tightly closed and protected from moisture and humidity.
- Keep ROZEREM and all medicines out of reach of children.

General Information about ROZEREM

- Medicines are sometimes prescribed for purposes other than those listed in a Medication Guide.
- Do not use ROZEREM for a condition for which it was not prescribed.
- Do not share ROZEREM with other people, even if you think they have the same symptoms that you have. It may harm them.

This Medication Guide summarizes the most important information about ROZEREM. If you would like more information, talk with your doctor. You can ask your doctor or pharmacist for information about ROZEREM that is written for healthcare professionals. For more information about ROZEREM, please call Takeda Pharmaceuticals America, Inc. at 1-877-TAKEDA-7 (1-877-825-3327) or visit www.rozerem.com.

What are the ingredients in ROZEREM?

Active Ingredient: ramelteon

Inactive Ingredients: lactose monohydrate, starch, hydroxypropyl cellulose, magnesium stearate, hypromellose, copovidone, titanium dioxide, yellow ferric oxide, polyethylene glycol 8000, and ink containing shellac and synthetic iron oxide black.

This Medication Guide has been approved by the U.S. Food and Drug Administration.

Distributed by:
Takeda Pharmaceuticals America, Inc.
Cambridge, MA 02142

ROZEREM is a registered trademark of Takeda Pharmaceutical Company Limited.

©2025 Takeda Pharmaceuticals U.S.A., Inc. All rights reserved.

ROZ014 R12 June 2025

PRINCIPAL DISPLAY PANEL - 8 mg Bottle Label

NDC 64764-805-30

30 Tablets

Rozerem®
(ramelteon tablets)
8 mg

Each film-coated tablet contains 8 mg
of ramelteon.

Dispense with Medication Guide
in package insert or at
www.rozerem.com

Takeda

Rx Only